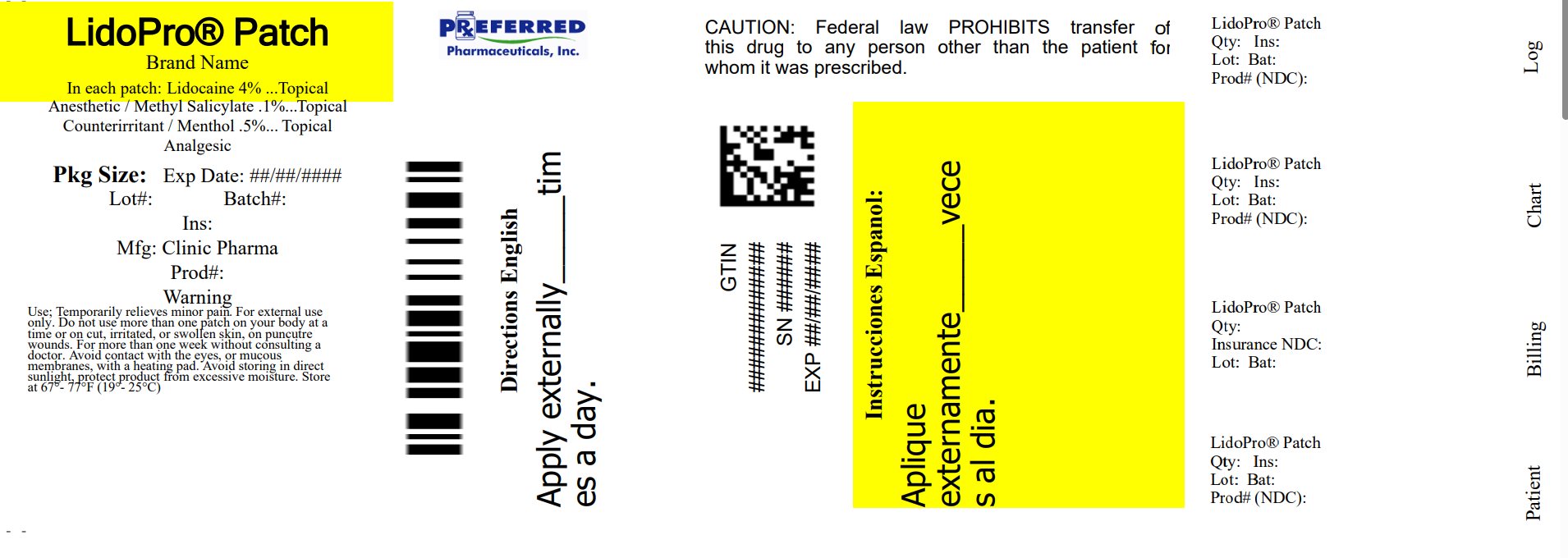 DRUG LABEL: LidoPro Patch
NDC: 68788-8594 | Form: PATCH
Manufacturer: Preferred Pharmaceuticals Inc.
Category: otc | Type: HUMAN OTC DRUG LABEL
Date: 20250716

ACTIVE INGREDIENTS: LIDOCAINE 4 mg/100 mg; MENTHOL, UNSPECIFIED FORM 0.5 mg/100 mg; METHYL SALICYLATE 0.1 mg/100 mg
INACTIVE INGREDIENTS: GLYCERIN; POLYACRYLIC ACID (250000 MW); POLYSORBATE 80; WATER

LidoPro Patch

Active Ingredient

Lidocaine 4%

Purpose

Topical Anesthetic

Active Ingredient

Menthol .5%

Purpose

Topical Analgesic

Active Ingredient

Methyl Salicylate .1%

Purpose

Topical Counterirritant

Uses

Temporarily relieves minor pain

Warnings

For external use only

Do not use

• more than one patch on your bidy at a time or on cuts, irritated, or swollen skin

• on puncture wounds

• for more than one week without consulting a doctor.

When using this product

- Use only as directed. Read and follow directions and warning on this packaging.
- Do not apply to wounds or damaged, broken, or irritated skin
- Avoid contact with the eyes or mucous membranes
- Do not bandage tightly or apply local heat (such as heating pads) to area of use
- Do not use at the same time as other topical analgesics
- Dispose of used patch in manner that always keeps product away from children and pets. Used patches still contain the drug product that can produce serious adverse effects if a child or pet chews or ingests this patch.

Stop use and ask a doctor if

- conditions worsens
- redness is present
- irritation develops
- symptoms persist for more than 7 days or clear up and occur again within a few days
- you experience signs of injury, such as pain, swelling, or blistering where the product was applied

If pregnant or breast feeding,

ask health professional before use.

Keep out of reach of children and pets.

If swallowed, get medical help or contact a Poison Control Center right away.

DIRECTIONS

adults and children over 12 years:

- clean and dry the affected area
- remove patch from plastic liner and place on the affected area
- use 1 patch for up to 12 hours
- place used patch on the liner when not in use
- re-use the patch up to 2 times.

children 12 years or younger: ask a doctor

OTHER INGREDIENTS:

Vegan Glycerol, Polyacrylate, Aqua. Polysorbate 80

Principal Display Panel

LidoPro patch

Relabeled By: Preferred Pharmaceuticals Inc.

NDC 68788-8594-3